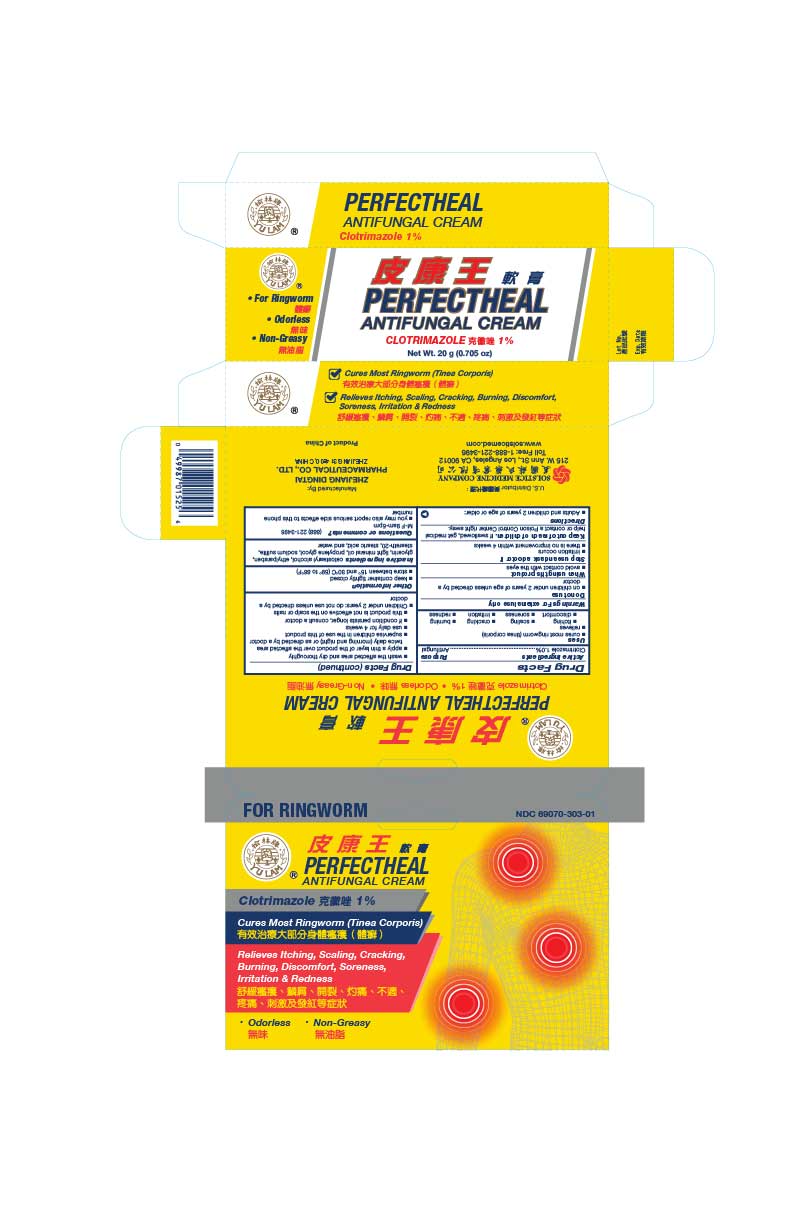 DRUG LABEL: PerfectHeal Antifungal
NDC: 69070-303 | Form: CREAM
Manufacturer: Zhejiang Dingtai Pharmaceutical Co., Ltd
Category: otc | Type: HUMAN OTC DRUG LABEL
Date: 20251110

ACTIVE INGREDIENTS: CLOTRIMAZOLE 1 g/100 g
INACTIVE INGREDIENTS: CETOSTEARYL ALCOHOL; ETHYLPARABEN; GLYCERIN; LIGHT MINERAL OIL; PROPYLENE GLYCOL; SODIUM SULFITE; STEARETH-20; STEARIC ACID; WATER

Drug Facts

Active ingredient
Clotrimazole 1.0%

Purpose
Antifungal

Uses
cures most ringworm (tinea corporis)
relieves
itching
scaling
cracking
burning
discomfort
soreness
irritation
redness

Warnings
For external use only

Do not use
on children under 2 years of age unless directed by a doctor

When using this product
avoid contact with the eyes

Stop use and ask a doctor if
irritation occurs
there is no improvement within 4 weeks

Keep out of reach of children.If swallowed, get medical help or contact a Poison Control Center right away.

Directions
Adults and children 2 years of age or older:
wash the affected area and dry thoroughly
apply a thin layer of the product over the affected area twice daily (morning and night) or as directed by a doctor
supervise children in the use of this product  use daily for 4 weeks
if condition persists longer, consult a doctor
this product is not effective on the scalp or nails
Children under 2 years: do not use unless directed by a doctor

Other information
keep container tightly closed
store between 15 and 30 C (59 to 86 F)

INACTIVE INGREDIENT

Inactive ingredientscetostearyl alcohol, ethylparaben, glycerin, light mineral oil, propylene glycol, sodium sulfite, steareth-20, stearic acid, and water

Questions or comments?(888) 221-3496 M-F 9am-5pm
you may also report serious side effects to this phone number

PACKAGE LABEL

PerfectHeal Antifungal
Clotrimazole 1%
Antifungal Cream
Net Wt. 10 g (1/3 oz)
NDC 69070-303-01